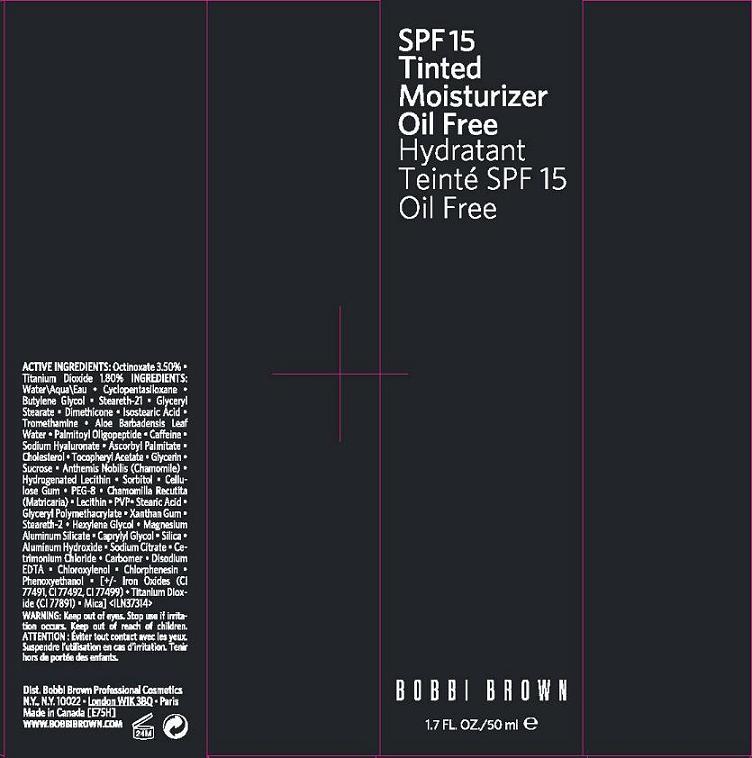 DRUG LABEL: TINTED MOISTURIZER
NDC: 64141-010 | Form: LIQUID
Manufacturer: Bobbi Brown Professional Cosmetics Inc.
Category: otc | Type: HUMAN OTC DRUG LABEL
Date: 20110309

ACTIVE INGREDIENTS: OCTINOXATE 3.5 mL/100 mL; TITANIUM DIOXIDE 1.8 mL/100 mL
INACTIVE INGREDIENTS: CYCLOMETHICONE 5; WATER; BUTYLENE GLYCOL; GLYCERYL MONOSTEARATE; DIMETHICONE; ISOSTEARIC ACID; PHENOXYETHANOL; CHOLESTEROL; .ALPHA.-TOCOPHEROL ACETATE, DL-; GLYCERIN

ACTIVE INGREDIENT

ACTIVE INGREDIENTS: OCTINOXATE 3.50% [] TITANIUM DIOXIDE 1.80%

INACTIVE INGREDIENT

INACTIVE INGREDIENTS: WATER [] CYCLOPENTASILOXANE [] BUTYLENE GLYCOL [] STEARETH-21 [] GLYCERYL STEARATE [] DIMETHICONE [] ISOSTEARIC ACID [] TROMETHAMINE [] ALOE BARBADENSIS LEAF WATER [] PALMITOYL OLIGOPEPTIDE [] CAFFEINE [] SODIUM HYALURONATE [] ASCORBYL PALMITATE [] CHOLESTEROL [] TOCOPHERYL ACETATE [] GLYCERIN [] SUCROSE [] ANTHEMIS NOBILIS (CHAMOMILE) [] HYDROGENATED LECITHIN [] SORBITOL [] CELLULOSE GUM [] PEG-8 [] CHAMOMILLA RECUTITA (MATRICARIA) [] LECITHIN [] PVP [] STEARIC ACID [] GLYCERYL POLYMETHACRYLATE [] XANTHAN GUM [] STEARETH-2 [] HEXYLENE GLYCOL [] MAGNESIUM ALUMINUM SILICATE [] CAPRYLYL GLYCOL [] SILICA [] ALUMINUM HYDROXIDE [] SODIUM CITRATE [] CETRIMONIUM CHLORIDE [] CARBOMER [] DISODIUM EDTA [] CHLOROXYLENOL [] CHLORPHENESIN [] PHENOXYETHANOL [] [+/- IRON OXIDES (CI 77491, CI 77492, CI 77499) [] TITANIUM DIOXIDE (CI 77891) [] MICA]

WARNINGS

WARNING: KEEP OUT OF EYES. STOP USE IF IRRITATION OCCURS.

KEEP OUT OF REACH OF CHILDREN

PHARMACOKINETICS

PRINCIPAL DISPLAY PANEL:

BOBBI BROWN

SPF 15
TINTED MOISTURIZER
OIL FREE
1.7 FL OZ/50 ML
BOBBI BROWN PROF COS DISTR
NY NY